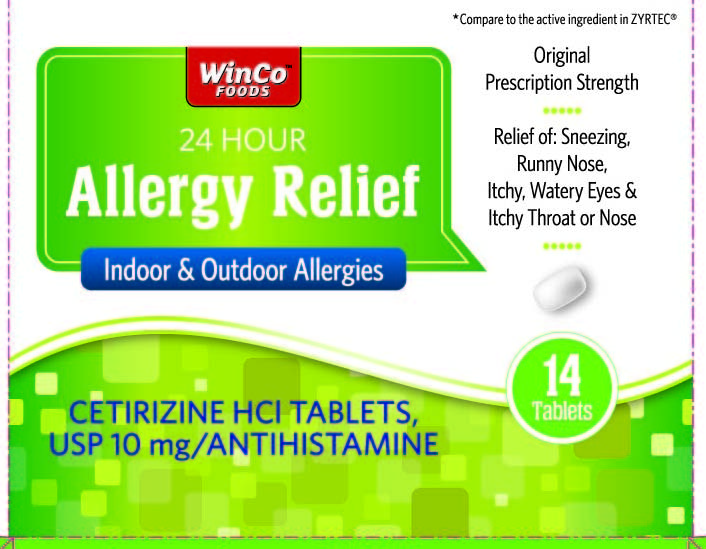 DRUG LABEL: Cetirizine Hydrochloride
NDC: 67091-247 | Form: TABLET
Manufacturer: WinCo Foods, LLC
Category: otc | Type: HUMAN OTC DRUG LABEL
Date: 20141215

ACTIVE INGREDIENTS: CETIRIZINE HYDROCHLORIDE 10 mg/1 1
INACTIVE INGREDIENTS: LACTOSE MONOHYDRATE; MAGNESIUM STEARATE; STARCH, CORN; TALC; TITANIUM DIOXIDE; HYPROMELLOSES; POLYETHYLENE GLYCOLS; POVIDONES

Drug Facts

ACTIVE INGREDIENT (IN EACH TABLET)

Cetirizine HCl, USP 10 mg

PURPOSE

Antihistamine

USES

temporarily relieves these symptoms due to hay fever or other upper respiratory allergies:

- runny nose
- sneezing
- itchy, watery eyes
- itching of the nose or throat

WARNINGS

Do not use

if you have ever had an allergic reaction to this product or any of its ingredients or to an antihistamine containing hydroxyzine.

Ask a doctor before use if you have

liver or kidney disease. Your doctor should determine if you need a different dose.

Ask a doctor or pharmacist before use if you are

taking tranquilizers or sedatives.

When using this product

- drowsiness may occur
- avoid alcoholic drinks
- alcohol, sedatives, and tranquilizers may increase drowsiness
- be careful when driving a motor vehicle or operating machinery

Stop use and ask a doctor if

an allergic reaction to this product occurs. Seek medical help right away.

If pregnant or breast-feeding:

- if breast-feeding: not recommended
- if pregnant: ask a health professional before use.

Keep out of reach of children.

In case of overdose, get medical help or contact a Poison Control Center right away (1-800-222-1222).

DIRECTIONS

adults and children 6 years and over: one 10 mg tablet once daily; do not take more than one 10 mg tablet in 24 hours. A 5 mg product may be appropriate for less severe symptoms.

adults 65 years and over ask a doctor

children under 6 years of age ask a doctor

consumers with liver or kidney disease ask a doctor

OTHER INFORMATION

- TAMPER EVIDENT: DO NOT USE IF BLISTER UNITS ARE TORN, BROKEN OR SHOW ANY SIGNS OF TAMPERING (for blister cartons only)
- store between 20° to 25° C (68° to 77° F)

INACTIVE INGREDIENTS

corn starch, hypromellose, lactose monohydrate, magnesium stearate, polyethylene glycol, povidone, talc, titanium dioxide

QUESTIONS?

or to report an adverse event call 800-824-1706 Monday - Friday 9am - 4pm MST

KEEP THE CARTON. IT CONTAINS IMPORTANT INFORMATION. See end panel for expiration date.

DISTRIBUTED BY:

WINCO FOODS, LLC, BOISE, ID 83704

5113308/0914

PRINCIPAL DISPLAY PANEL

Compare to the active ingredient of ZYRTEC®

WinCo FOODS

24 Hour

Allergy Relief

Indoor & Outdoor Allergies

Original Prescription Strength

Relief of:

- Sneezing
- Runny Nose
- Itchy, Watery Eyes
- Itchy Throat or Nose

CETIRIZINE HCL TABLETS, USP 10 mg/ANTIHISTAMINE

14 Tablets